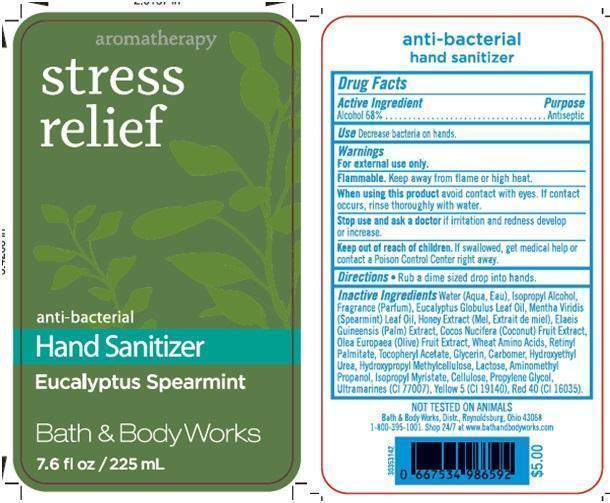 DRUG LABEL: Anti-Bacterial Hand Sanitizer
NDC: 62670-4780 | Form: GEL
Manufacturer: Bath & Body Works, Inc.
Category: otc | Type: HUMAN OTC DRUG LABEL
Date: 20150120

ACTIVE INGREDIENTS: ALCOHOL 68 mL/100 mL
INACTIVE INGREDIENTS: WATER

ACTIVE INGREDIENT

Alcohol 68%

PURPOSE

Antiseptic

USE

Decrease bacteria on hands.

WARNINGS

For external use only.

FLAMMABLE

Keep away from flame or high heat.

WHEN USING THIS PRODUCT

avoid contact with eyes. If contact occurs, rinse thoroughly with water.

STOP USE AND ASK A DOCTOR

if irritation and redness develop or increase.

KEEP OUT OF REACH OF CHILDREN

If swallowed, get medical help or contact a Poison Control Center right away.

DIRECTIONS

- Rub a dime sized drop into hands.

INACTIVE INGREDIENTS

Water (Aqua, Eau), Isopropyl Alcohol, Fragrance (Parfum), Eucalyptus Globulus Leaf Oil, Mentha Viridis (Spearmint) Leaf Oil, Honey Extract (Mel, Extrait de miel), Elaeis Guineensis (Palm) Extract, Cocos Nucifera (Coconut) Fruit Extract, Olea Europaea (Olive) Fruit Extract, Wheat Amino Acids, Retinyl Palmitate, Tocopheryl Acetate, Glycerin, Carbomer, Hydroxyethyl Urea, Hydroxypropyl Methylcellulose, Lactose, Aminomethyl Propanol, Isopropyl Myristate, Cellulose, Propylene Glycol, Ultramarines (CI 77007), Yellow 5 (CI 19140), Red 40 (CI 16035).

COMPANY INFORMATION

Bath & Body Works, Distr.

Reynoldsburg, Ohio 43068

1-800-395-1001

www.bathandbodyworks.com